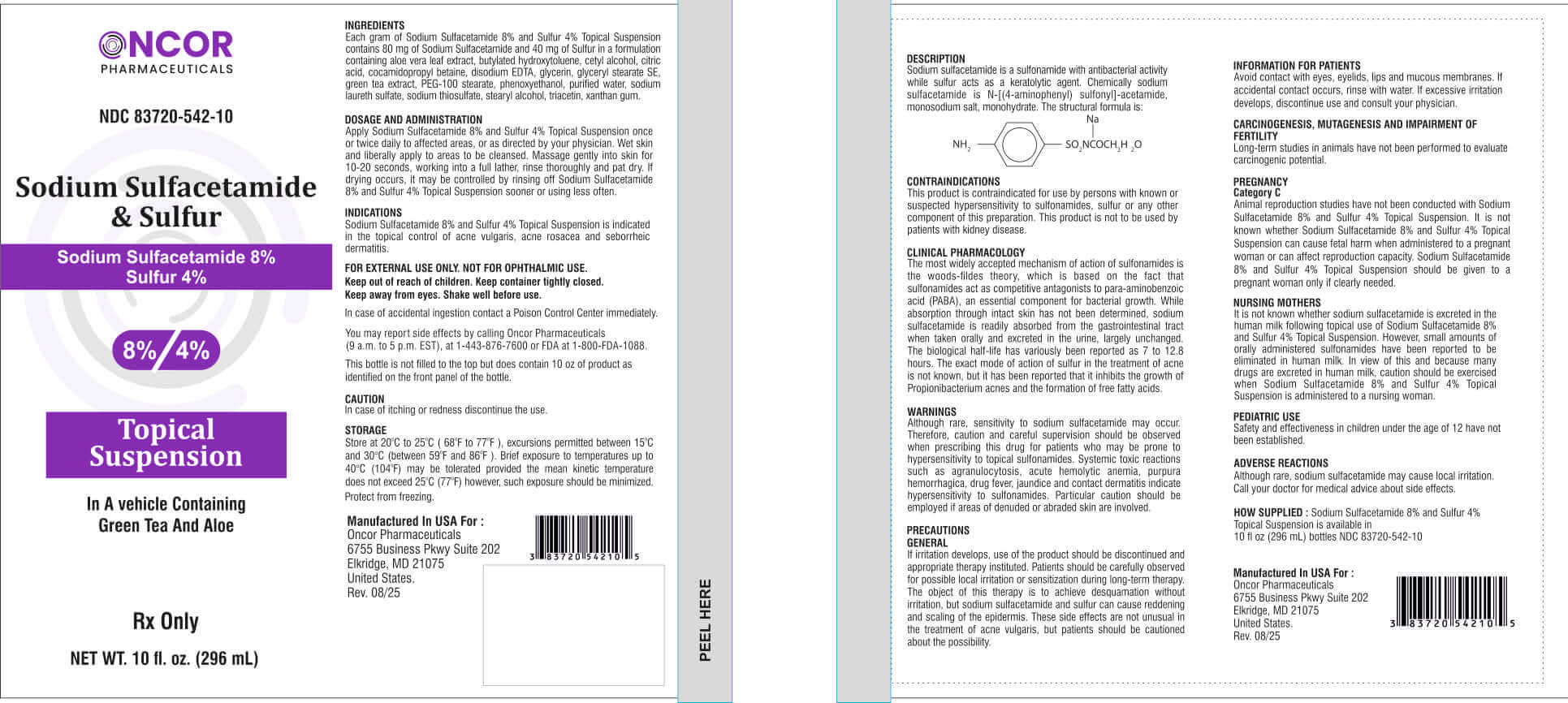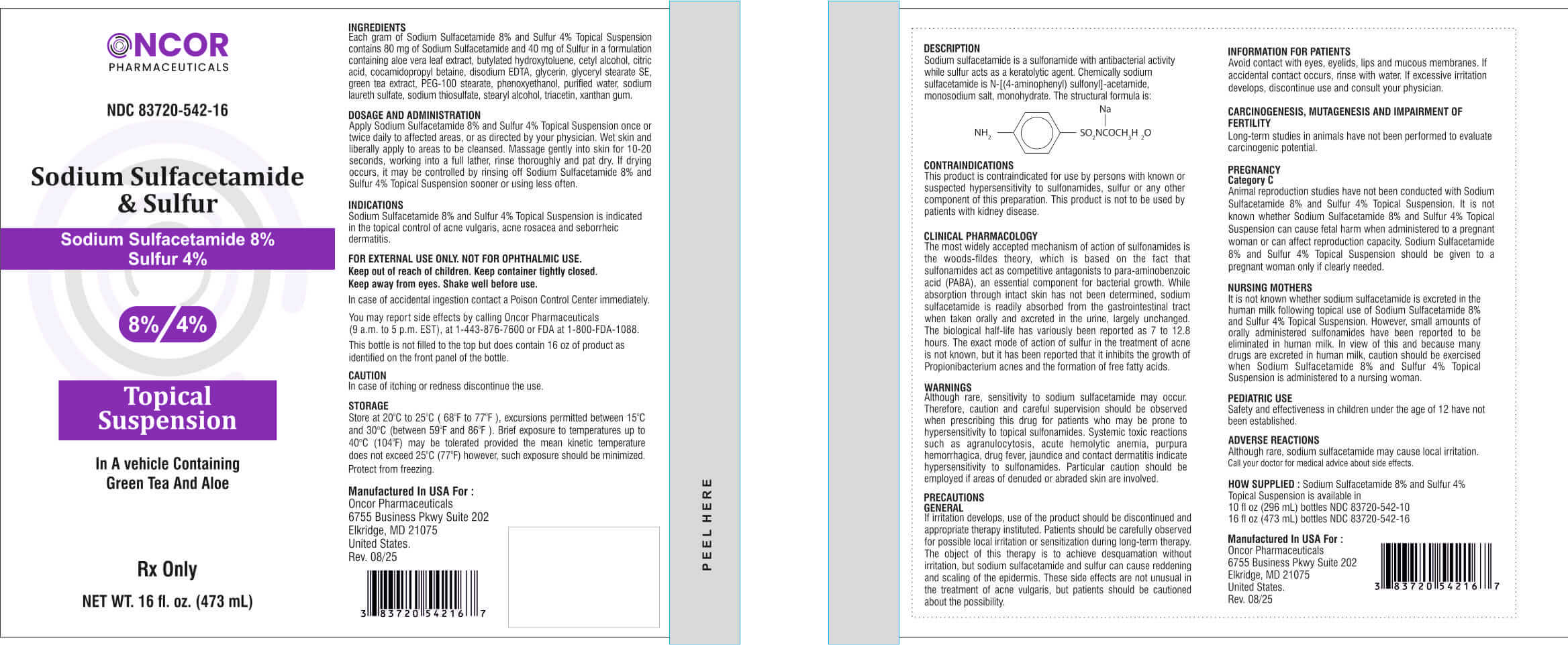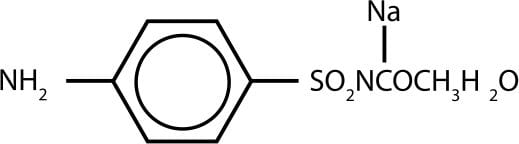 DRUG LABEL: Sodium Sulfacetamide 8%  Sulfur 4% CLEANSER
NDC: 83720-542 | Form: LIQUID
Manufacturer: Oncor Pharmaceuticals
Category: prescription | Type: HUMAN PRESCRIPTION DRUG LABEL
Date: 20260211

ACTIVE INGREDIENTS: SULFACETAMIDE SODIUM 80 mg/1 mL; SULFUR 40 mg/1 mL
INACTIVE INGREDIENTS: ALOE VERA LEAF; BUTYLATED HYDROXYTOLUENE; CETYL ALCOHOL; CITRIC ACID MONOHYDRATE; COCAMIDOPROPYL BETAINE; EDETATE DISODIUM; GLYCERIN; GLYCERYL STEARATE SE; GREEN TEA LEAF; PEG-100 STEARATE; PHENOXYETHANOL; WATER; SODIUM LAURYL SULFATE; SODIUM THIOSULFATE; STEARYL ALCOHOL; TRIACETIN; XANTHAN GUM

Sodium Sulfacetamide 8% Sulfur 4% Topical Suspension

In A Vehical Containing Green Tea And Aloe
Rx Only

DESCRIPTION

Each gram of Sodium Sulfacetamide 8% and Sulfur 4% Topical Suspension contains 80 mg of sodium sulfacetamide and 40 mg of sulfur in a formulation containing Aloe vera leaf extract, Butylated hydroxytoluene, Cetyl alcohol, Citric acid, Cocamidopropyl betaine, Disodium EDTA, Glycerin, Glyceryl stearate SE, Green tea extract, PEG-100 stearate, Phenoxyethanol, Purified water, Sodium laureth sulfate, Sodium thiosulfate, Stearyl alcohol, Triacetin, Xanthan gum.

Sodium sulfacetamide is a sulfonamide with antibacterial activity while sulfur acts as a keratolytic agent. Chemica ly sodium sulfacetamide is N-[(4-aminophenyl) sulfonyl]-acetamide, monosodium salt, monohydrate. The structural formula is:

INDICATIONS

Sodium Sulfacetamide 8% and Sulfur 4% Topical Suspension is indicated in the topical control of acne vulgaris, acne rosacea and seborrheic dermatitis.

FOR EXTERNAL USE ONLY. NOT FOR OPHTHALMIC USE.
Keep out of reach of children. Keep container tightly closed.
Shake well before use.

OTHER SAFETY INFORMATION

In case of accidental ingestion contact a Poison Control Center immediately. Keep container tightly closed.

You may report side effects by ca ling Oncor Pharmaceuticals (9 a.m. to 5 p.m. EST), at 1-443-876-7600 or FDA at 1-800-FDA-1088.

PRECAUTIONS

Incase of itching or redness discontinue the use.

STORAGE

Store at 20oC to 25oC (68oF to 77oF), excursions permitted between 15oC and 30oC (between 59oF and 86oF). Brief exposure to temperatures up to 40°C (104oF) may be tolerated provided the mean kinetic temperature does not exceed 25oC (77oF) however, such exposure should be minimized.

Protect from freezing.

DOSAGE AND ADMINISTRATION

Apply Sodium Sulfacetamide 8% and Sulfur 4% Topical Suspension once or twice daily to affected areas, or as directed by your physician. Wet skin and liberally apply to areas to be cleansed. Massage gently into skin for 10-20 seconds, working into a full lather, rinse thoroughly and pat dry. If drying occurs, it may be controlled by rinsing off Sodium Sulfacetamide 8% and Sulfur 4% Topical Suspension sooner or using less often.

CONTRAINDICATIONS

This product is contraindicated for use by persons with known or suspected hypersensitivity to sulfonamides, sulfur or any other component of this preparation. This product is not to be used by patients with kidney disease.

CLINICAL PHARMACOLOGY

The most widely accepted mechanism of action of sulfonamides is the woods fildes theory, which is based on the fact that sulfonamides act as competitive antagonists to para-aminobenzoic acid (PABA), an essential component for bacterial growth. While absorption through intact skin has not been determined, sodium sulfacetamide is readily absorbed from the gastrointestinal tract when taken orally and excreted in the urine, largely unchanged. The biological half-life has variously been reported as 7 to 12.8 hours. The exact mode of action of sulfur in the treatment of acne is not known, but it has been reported that it inhibits the growth of Propionibacterium acnes and the formation of free fatty acids.

WARNINGS

Although rare, sensitivity to sodium sulfacetamide may occur. Therefore, caution and careful supervision should be observed when prescribing this drug for patients who may be prone to hypersensitivity to topical sulfonamides. Systemic toxic reactions such as agranulocytosis, acute hemolytic anemia, purpura hemorrhagica, drug fever, jaundice and contact dermatitis indicate hypersensitivity to sulfonamides. Particular caution should be employed if areas of denuded or abraded skin are involved.

PRECAUTIONSGENERAL

If irritation develops, use of the product should be discontinued and appropriate therapy instituted. Patients should be carefully observed for possible local irritation or sensitization during long-term therapy. The object of this therapy is to achieve desquamation without irritation, but sodium sulfacetamide and sulfur can cause reddening and scaling of the epidermis. These side effects are not unusual in the treatment of acne vulgaris, but patients should be cautioned about the possibility.

INFORMATION FOR PATIENTS

Avoid contact with eyes, eyelids, lips and mucous membranes. If accidental contact occurs, rinse with water. If excessive irritation develops, discontinue use and consult your physician.

CARCINOGENESIS, MUTAGENESIS AND IMPAIRMENT OF FERTILITY

Long-term studies in animals have not been performed to evaluate carcinogenic potential.

PREGNANCYCategory C

Animal reproduction studies have not been conducted with Sodium Sulfacetamide 8% and Sulfur 4% Topical Suspension. It is not known whether
Sodium Sulfacetamide 8% and Sulfur 4% Topical Suspension can cause fetal harm when administered to a pregnant woman or can affect reproduction capacity. Sodium Sulfacetamide 8% and Sulfur 4% Topical Suspension should be given to a pregnant woman only if clearly needed.

NURSING MOTHERS

It is not known whether sodium sulfacetamide is excreted in the human milk following topical use of Sodium Sulfacetamide 8% and Sulfur 4% Topical Suspension. However, small amounts of orally administered sulfonamides have been reported to be eliminated in human milk. In view of this and because many drugs are excreted in human milk, caution should be exercised when Sodium Sulfacetamide 8% and Sulfur 4% Topical Suspension is administered to a nursing woman.

PEDIATRIC USE

Safety and effectiveness in children under the age of 12 have not been established.

ADVERSE REACTIONS

Although rare, sodium sulfacetamide may cause local irritation. Call your doctor for medical advice about side effects.

HOW SUPPLIED

Sodium Sulfacetamide 8% and Sulfur 4% Topical Suspension is available in
10 fl oz (296 mL) bottles NDC 83720-542-10.

PACKAGE LABEL

Manufactured In USA For :

Oncor Pharmaceuticals
6755 Business Pkwy Suite 202
Elkridge, MD 21075
United States.
Rev. 08/25